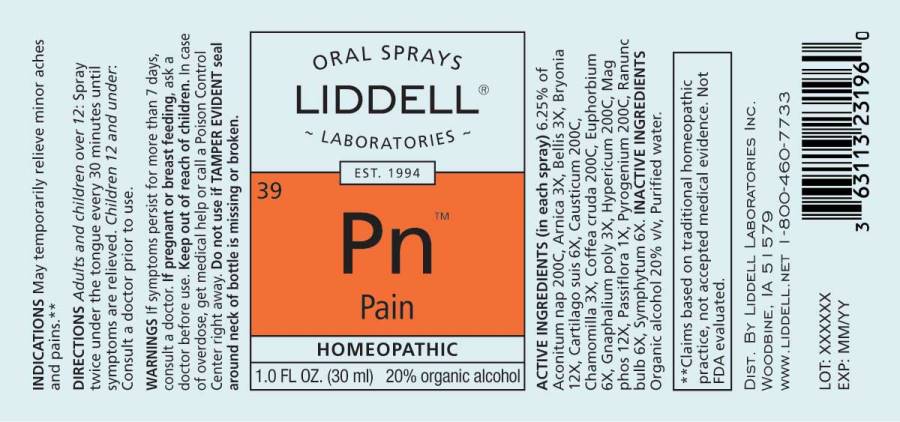 DRUG LABEL: Pain
NDC: 50845-0265 | Form: SPRAY
Manufacturer: Liddell Laboratories, Inc.
Category: homeopathic | Type: HUMAN OTC DRUG LABEL
Date: 20231219

ACTIVE INGREDIENTS: ACONITUM NAPELLUS WHOLE 200 [hp_C]/1 mL; ARNICA MONTANA WHOLE 3 [hp_X]/1 mL; BELLIS PERENNIS WHOLE 3 [hp_X]/1 mL; BRYONIA ALBA ROOT 12 [hp_X]/1 mL; SUS SCROFA CARTILAGE 6 [hp_X]/1 mL; CAUSTICUM 200 [hp_C]/1 mL; MATRICARIA CHAMOMILLA WHOLE 3 [hp_X]/1 mL; ARABICA COFFEE BEAN 200 [hp_C]/1 mL; EUPHORBIA RESINIFERA RESIN 6 [hp_X]/1 mL; PSEUDOGNAPHALIUM OBTUSIFOLIUM WHOLE 3 [hp_X]/1 mL; HYPERICUM PERFORATUM WHOLE 200 [hp_C]/1 mL; MAGNESIUM PHOSPHATE, DIBASIC TRIHYDRATE 12 [hp_X]/1 mL; PASSIFLORA INCARNATA FLOWERING TOP 1 [hp_X]/1 mL; RANCID BEEF 200 [hp_C]/1 mL; RANUNCULUS BULBOSUS WHOLE 6 [hp_X]/1 mL; COMFREY ROOT 6 [hp_X]/1 mL
INACTIVE INGREDIENTS: WATER; ALCOHOL

DRUG FACTS:

ACTIVE INGREDIENTS:

(in each spray): 6.25% of Aconitum Napellus 200C, Arnica Montana 3X, Bellis Perennis 3X, Bryonia (Alba)12X, Cartilago Suis 6X, Causticum 200X, Chamomilla 3X, Coffea Cruda 200C, Euphorbium Officinarum 6X, Gnaphalium Polycephalum 3X, Hypericum Perforatum 200C, Magnesia Phosphorica 12X, Passiflora Incarnata 1X, Pyrogenium 200C, Ranunculus Bulbosus 6X, Symphytum Officinale 6X.

INDICATIONS:

May temporarily relieve minor aches and pains.**

**Claims based on traditional homeopathic practice, not accepted medical evidence. Not FDA evaluated.

WARNINGS:

If symptoms persist for more than 7 days, consult a doctor.

If pregnant or breast feeding, ask a doctor before use.

Keep out of reach of children. In case of overdose, get medical help or call a Poison Control Center right away.

Do not use if TAMPER EVIDENT seal around neck of bottle is missing or broken.

KEEP OUT OF REACH OF CHILDREN:

In case of overdose, get medical help or call a Poison Control Center right away.

DIRECTIONS:

Adults and children over 12: Spray twice under the tongue every 30 minutes until symptoms are relieved.

Children 12 and under: Consult a doctor prior to use.

INDICATIONS:

May temporarily relieve minor aches and pains.**

**Claims based on traditional homeopathic practice, not accepted medical evidence. Not FDA evaluated.

INACTIVE INGREDIENTS:

Organic alcohol 20% v/v, Purified water.

QUESTIONS:

DIST. BY LIDDELL LABORATORIES INC.

WOODBINE, IA 51579

WWW.LIDDELL.NET 1-800-460-7733

PACKAGE LABEL DISPLAY:

ORAL SPRAYS
LIDDELL
LABORATORIES
EST. 1994
39 Pn

Pain

HOMEOPATHIC
1.0 FL. OZ. (30 ml)